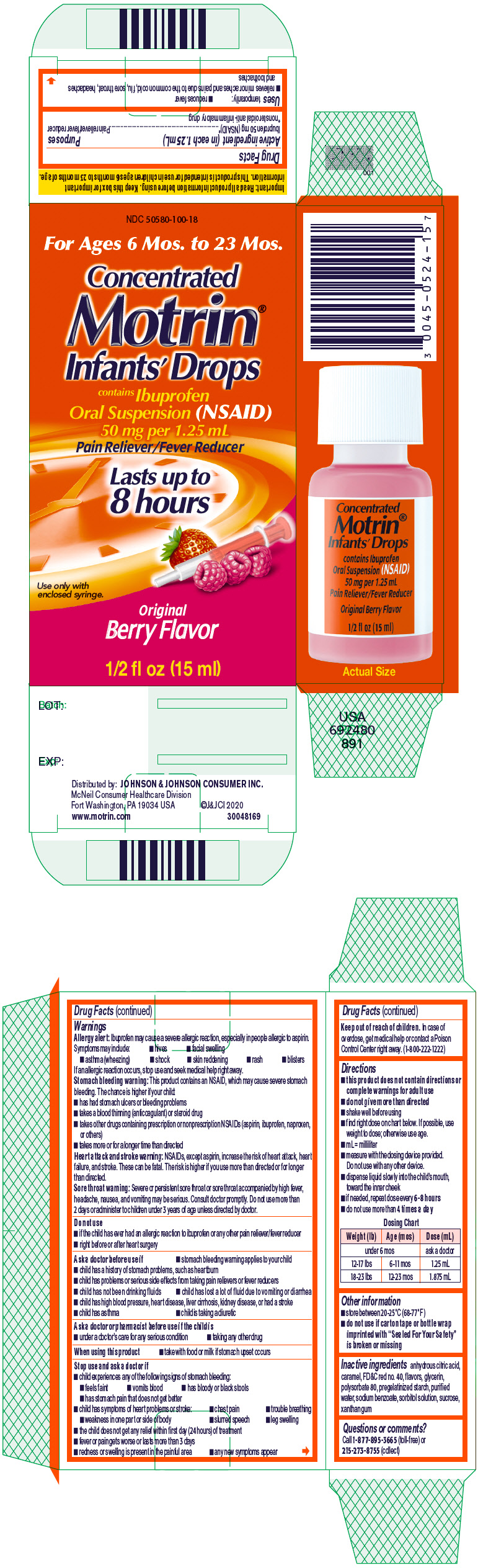 DRUG LABEL: Infants Motrin
NDC: 50580-100 | Form: SUSPENSION/ DROPS
Manufacturer: Kenvue Brands LLC
Category: otc | Type: HUMAN OTC DRUG LABEL
Date: 20250116

ACTIVE INGREDIENTS: IBUPROFEN 50 mg/1.25 mL
INACTIVE INGREDIENTS: ANHYDROUS CITRIC ACID; CARAMEL; FD&C RED NO. 40; GLYCERIN; POLYSORBATE 80; WATER; SODIUM BENZOATE; SORBITOL SOLUTION; SUCROSE; XANTHAN GUM

Infants Motrin

Drug Facts

Active ingredient (in each 1.25 mL)

Ibuprofen 50 mg (NSAID) [nonsteroidal anti-inflammatory drug]

Purposes

Pain reliever/fever reducer

Uses

temporarily:

- reduces fever
- relieves minor aches and pains due to the common cold, flu, sore throat, headaches and toothaches

Warnings

Allergy alert

Ibuprofen may cause a severe allergic reaction, especially in people allergic to aspirin. Symptoms may include:

- hives
- facial swelling
- asthma (wheezing)
- shock
- skin reddening
- rash
- blisters

If an allergic reaction occurs, stop use and seek medical help right away.

Stomach bleeding warning

This product contains an NSAID, which may cause severe stomach bleeding. The chance is higher if your child:

- has had stomach ulcers or bleeding problems
- takes a blood thinning (anticoagulant) or steroid drug
- takes other drugs containing prescription or nonprescription NSAIDs (aspirin, ibuprofen, naproxen, or others)
- takes more or for a longer time than directed

Heart attack and stroke warning

NSAIDs, except aspirin, increase the risk of heart attack, heart failure, and stroke. These can be fatal. The risk is higher if you use more than directed or for longer than directed.

Sore throat warning

Severe or persistent sore throat or sore throat accompanied by high fever, headache, nausea, and vomiting may be serious. Consult doctor promptly. Do not use more than 2 days or administer to children under 3 years of age unless directed by doctor.

Do not use

- if the child has ever had an allergic reaction to ibuprofen or any other pain reliever/fever reducer
- right before or after heart surgery

Ask a doctor before use if

- stomach bleeding warning applies to your child
- child has a history of stomach problems, such as heartburn
- child has problems or serious side effects from taking pain relievers or fever reducers
- child has not been drinking fluids
- child has lost a lot of fluid due to vomiting or diarrhea
- child has high blood pressure, heart disease, liver cirrhosis, kidney disease, or had a stroke
- child has asthma
- child is taking a diuretic

Ask a doctor or pharmacist before use if the child is

- under a doctor's care for any serious condition
- taking any other drug

When using this product

- take with food or milk if stomach upset occurs

Stop use and ask a doctor if

- child experiences any of the following signs of stomach bleeding:
  - feels faint
  - vomits blood
  - has bloody or black stools
  - has stomach pain that does not get better
- child has symptoms of heart problems or stroke:
  - chest pain
  - trouble breathing
  - weakness in one part or side of body
  - slurred speech
  - leg swelling
- the child does not get any relief within first day (24 hours) of treatment
- fever or pain gets worse or lasts more than 3 days
- redness or swelling is present in the painful area
- any new symptoms appear

Keep out of reach of children. In case of overdose, get medical help or contact a Poison Control Center right away. (1-800-222-1222)

Directions

- this product does not contain directions or complete warnings for adult use
- do not give more than directed
- shake well before using
- find right dose on chart below. If possible, use weight to dose; otherwise use age.
- mL = milliliter
- measure with the dosing device provided. Do not use with any other device.
- dispense liquid slowly into the child's mouth, toward the inner cheek
- if needed, repeat dose every 6-8 hours
- do not use more than 4 times a day

Dosing Chart
Weight (lb) | Age (mos) | Dose (mL)
under 6 mos |  | ask a doctor
12-17 lbs | 6-11 mos | 1.25 mL
18-23 lbs | 12-23 mos | 1.875 mL

Other information

- store between 20-25°C (68-77°F)
- do not use if carton tape or bottle wrap imprinted with "Sealed For Your Safety" is broken or missing

Inactive ingredients

anhydrous citric acid, caramel, FD&C red no. 40, flavors, glycerin, polysorbate 80, pregelatinized starch, purified water, sodium benzoate, sorbitol solution, sucrose, xanthan gum

Questions or comments?

Call 1-877-895-3665 (toll-free) or 215-273-8755 (collect)

PRINCIPAL DISPLAY PANEL

NDC 50580-100-18

For Ages 6 Mos. to 23 Mos.

Concentrated
Motrin®
Infants' Drops
contains Ibuprofen
Oral Suspension (NSAID)
50 mg per 1.25 mL
Pain Reliever/Fever Reducer

Lasts up to
8 hours

Use only with
enclosed syringe.

Original
Berry Flavor

1/2 fl oz (15 ml)